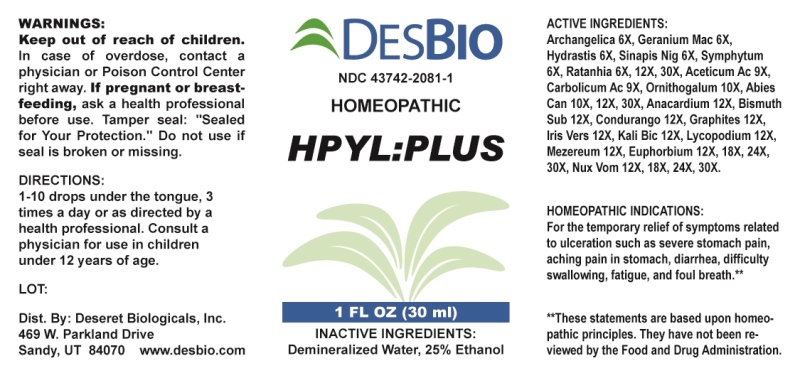 DRUG LABEL: HPYL PLUS
NDC: 43742-2081 | Form: LIQUID
Manufacturer: Deseret Biologicals, Inc.
Category: homeopathic | Type: HUMAN OTC DRUG LABEL
Date: 20231012

ACTIVE INGREDIENTS: ANGELICA ARCHANGELICA ROOT 6 [hp_X]/1 mL; GERANIUM MACULATUM ROOT 6 [hp_X]/1 mL; GOLDENSEAL 6 [hp_X]/1 mL; BLACK MUSTARD SEED 6 [hp_X]/1 mL; COMFREY ROOT 6 [hp_X]/1 mL; KRAMERIA LAPPACEA ROOT 6 [hp_X]/1 mL; ACETIC ACID 9 [hp_X]/1 mL; PHENOL 9 [hp_X]/1 mL; ORNITHOGALUM UMBELLATUM WHOLE 10 [hp_X]/1 mL; TSUGA CANADENSIS FLOWER BUD 10 [hp_X]/1 mL; SEMECARPUS ANACARDIUM JUICE 12 [hp_X]/1 mL; BISMUTH SUBNITRATE 12 [hp_X]/1 mL; RUEHSSIA CUNDURANGO BARK 12 [hp_X]/1 mL; GRAPHITE 12 [hp_X]/1 mL; IRIS VERSICOLOR ROOT 12 [hp_X]/1 mL; POTASSIUM DICHROMATE 12 [hp_X]/1 mL; LYCOPODIUM CLAVATUM SPORE 12 [hp_X]/1 mL; DAPHNE MEZEREUM BARK 12 [hp_X]/1 mL; EUPHORBIA RESINIFERA RESIN 12 [hp_X]/1 mL; STRYCHNOS NUX-VOMICA SEED 12 [hp_X]/1 mL
INACTIVE INGREDIENTS: WATER; ALCOHOL

DRUG FACTS:

ACTIVE INGREDIENTS:

Angelica Archangelica 6X, Geranium Maculatum 6X, Hydrastis Canadensis 6X, Sinapis Nigra 6X, Symphytum Officinale 6X, Ratanhia 6X, 12X, 30X, Aceticum Acidum 9X, Carbolicum Acidum 9X, Ornithogalum Umbellatum 10X, Abies Canadensis 10X, 12X, 30X, Anacardium Orientale 12X, Bismuthum Subnitricum 12X, Condurango 12X, Graphites 12X, Iris Versicolor 12X, Kali Bichromicum 12X, Lycopodium Clavatum 12X, Mezereum 12X, Euphorbium Officinarum 12X, 18X, 24X, 30X, Nux Vomica 12X, 18X, 24X, 30X.

PURPOSE:

For the temporary relief of symptoms related to ulceration such as severe stomach pain, aching pain in stomach, diarrhea, difficulty swallowing, fatigue, and foul breath.**

**These statements are based upon homeopathic principles. They have not been reviewed by the Food and Drug Administration.

WARNINGS:

Keep out of reach of children. In case of overdose, contact a physician or a Poison Control Center right away.

If pregnant or breast-feeding, ask a health professional before use.

Tamper seal: "Sealed for Your Protection." Do not use if seal is broken or missing.

KEEP OUT OF REACH OF CHILDREN:

In case of overdose, contact a physician or Poison Control Center right away.

DIRECTIONS:

1-10 drops under the tongue, 3 times a day or as directed by a health professional. Consult a physician for use in children under 12 years of age.

INDICATIONS:

For the temporary relief of symptoms related to ulceration such as severe stomach pain, aching pain in stomach, diarrhea, difficulty swallowing, fatigue, and foul breath.**

**These statements are based upon homeopathic principles. They have not been reviewed by the Food and Drug Administration.

INACTIVE INGREDIENTS:

Demineralized Water, 25% Ethanol

QUESTIONS:

Dist. By: Deseret Biologicals, Inc.
469 W. Parkland Drive
Sandy, UT 84070 www.desbio.com

PACKAGE LABEL DISPLAY:

DesBio

NDC 43742-2081-1

HOMEOPATHIC

HPYL:PLUS

1 FL OZ (30 ml)